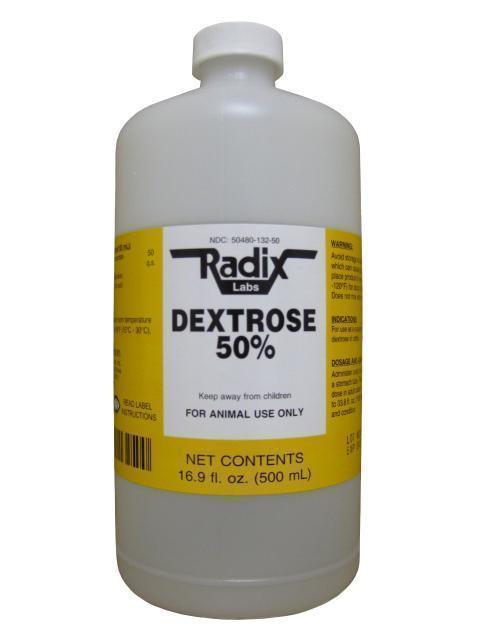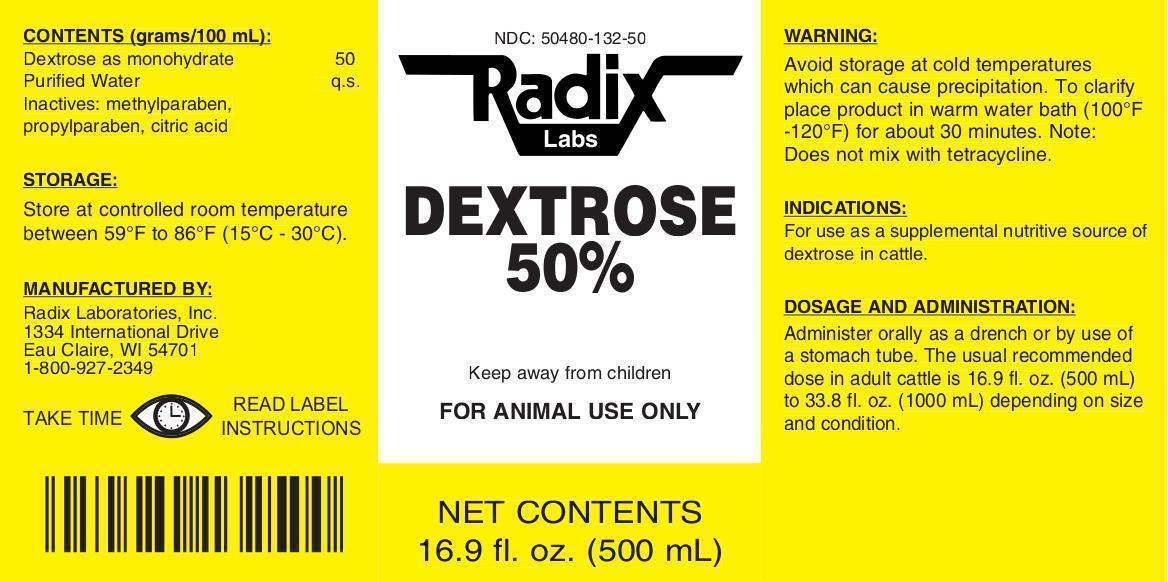 DRUG LABEL: Dextrose 50%
NDC: 50480-132 | Form: LIQUID
Manufacturer: Radix Laboratories, Inc.
Category: animal | Type: OTC ANIMAL DRUG LABEL
Date: 20141223

ACTIVE INGREDIENTS: DEXTROSE MONOHYDRATE 50 g/100 mL

DEXTROSE MONOHYDRATE

• CONTENTS (grams/100ml):

- Dextrose as monohydrate .....50

Inactives:

- Purified Water q.s.
- Methylparaben
- Propylparaben

Indications:

- For use as a supplemental nutritive source of dextrose in cattle.

Storage:

- Store at controlled room temperature between 59oF to 86oF (15oC -30oC).

Warnings:

- Avoid storage at cold temperatures which can cause product to become cloudy.
- To clarify place product in warm water bath (100oF-120oF) for about 30 minutes.

Dosage and administration:

- Administer orally as a drench or by use of a stomach tube.
- The usual recommended dose in adult cattle is 16.9 fl. oz (500mL) to 33.8 fl.oz (1000mL) depending on size and condition.

- Keep away from children.